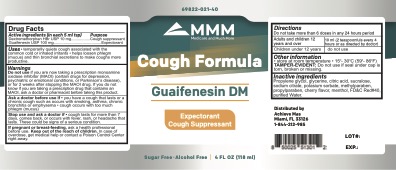 DRUG LABEL: MMM - Cough Formula Guaifenesin DM
NDC: 69822-021 | Form: LIQUID
Manufacturer: Southern Sales & Services, Inc
Category: otc | Type: HUMAN OTC DRUG LABEL
Date: 20210101

ACTIVE INGREDIENTS: GUAIFENESIN 100 mg/5 mL; DEXTROMETHORPHAN HYDROBROMIDE 10 mg/5 mL
INACTIVE INGREDIENTS: PROPYLPARABEN; PROPYLENE GLYCOL; GLYCERIN; CITRIC ACID MONOHYDRATE; SUCRALOSE; SODIUM CITRATE; METHYLPARABEN; CHERRY; FD&C RED NO. 40; MENTHOL; WATER; POTASSIUM SORBATE

MMM Cough Formula
Guaifenesin DM

Active ingredient (in each 5mI tsp.)
Dextromethorphan HBr USP 10 mg............Cough suppressant

Guaifenesin USP 100mg.............................Expectorant

PURPOSE

Expectorant, Cough Suppressant

Do not use if you are now taking a prescription monoamine oxidase inhibitor (MAOI) (certain drugs for depression, psychiatric or emotional conditions, or Parkinson’s disease), or for 2 weeks after stopping the MAOI drug. If you do not know if you are taking a prescription drug that contains an MAOI drug, ask a doctor or pharmacist before taking this product.

Ask a doctor before use if

you have a cough that lasts or a chronic cough such as occurs with smoking, asthma, chronic bronchitis or emphysema - cough occurs with too much phlegm (mucus)

Stop use and ask a doctor if

cough lasts for more than 7 days, comes back, or occurs with fever, rash, or headache that lasts. These could be signes of a serious condition.

If pregnant or breast-feeding

ask a health professional before use

Keep out of the reach of children

In case of oversdose, get medical help or contact a Poison Control Center right away.

INDICATIONS AND USAGE

See DOSAGE & ADMINISTRATION

DOSAGE AND ADMINISTRATION

Do not take more than 6 doses in any 24 hour period

adults and children 12 years and over...10ml (2 teaspoonfuls every 4 hours or as directed by doctor)

Children under 12 years...do not use

STORAGE AND HANDLING

Store at room temperature - 15°- 30°C (59°- 86°F)

TAMPER-EVIDENT : Do not use if seal under cap is torn, broken or missing.

INACTIVE INGREDIENT

Propylene glycol, glycerine, citric acid, sucralose, sodium citrate, potassium sorbate, methylparaben, propylparaben, cherry flavor, menthol, FD&C Red#40, purified Water

KEEP OUT OF REACH OF CHILDREN

MMM Cough Formula DM